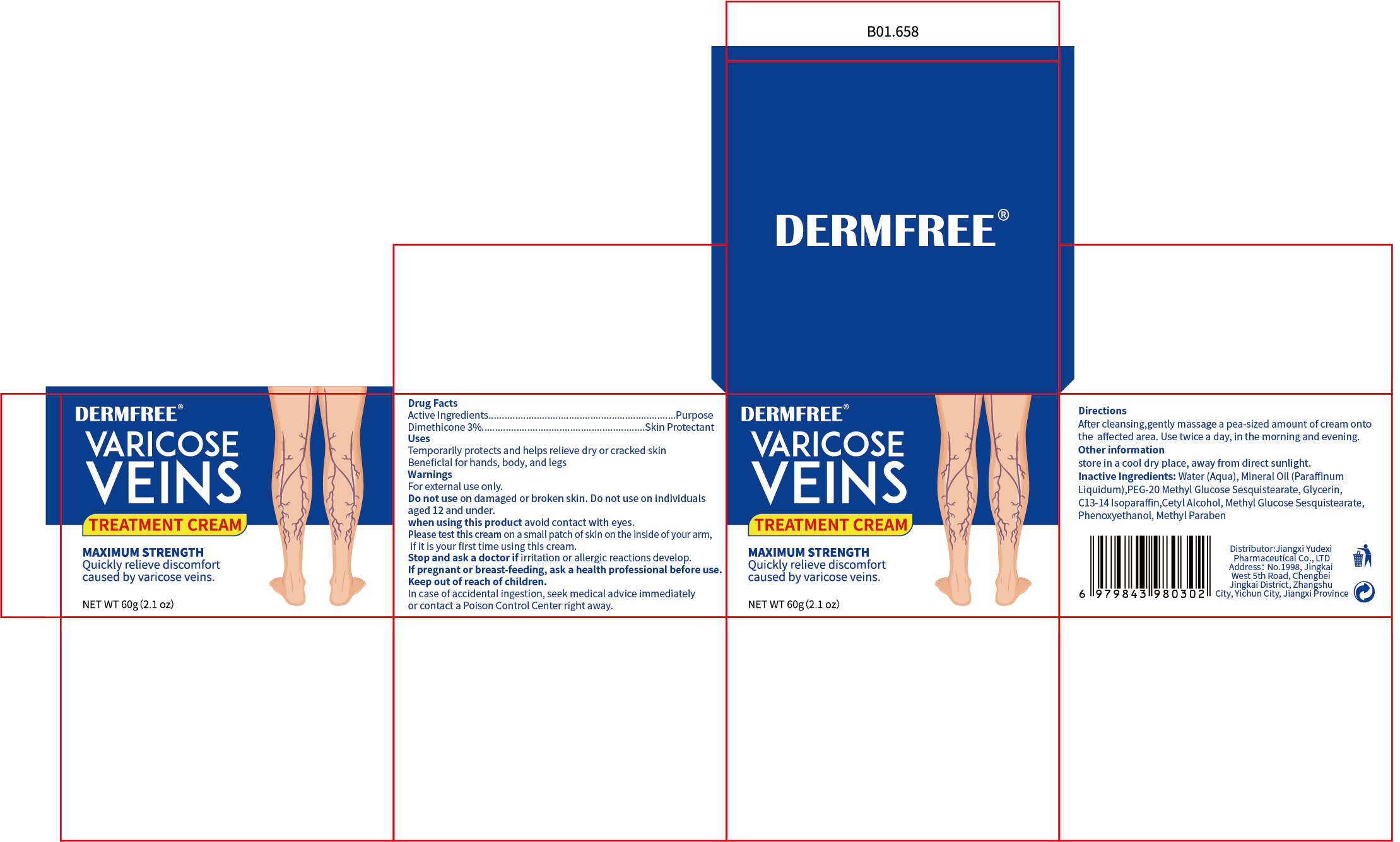 DRUG LABEL: DERMFREE VARICOSE VEINS
NDC: 85248-116 | Form: CREAM
Manufacturer: Jiangxi Yudexi Pharmaceutical Co., LTD
Category: otc | Type: HUMAN OTC DRUG LABEL
Date: 20260208

ACTIVE INGREDIENTS: DIMETHICONE 3 g/100 g
INACTIVE INGREDIENTS: GLYCERIN; METHYL GLUCOSE SESQUISTEARATE; CETYL ALCOHOL; C13-14 ISOPARAFFIN; PEG-20 METHYL GLUCOSE SESQUISTEARATE; METHYLPARABEN; MINERAL OIL; PHENOXYETHANOL; WATER

85248-116

Active Ingredient

Dimethicone 3%

Purpose

Skin Protectant

Use

Temporarily protects and helps relieve dry or cracked skin
Beneficlal for hands.body, and legs

Warnings

For external use only.

Do not use

on damaged or broken skin. Do not use on individuals aged 12 and under.

When Using

avoid contact with eyes.
Please test this cream on a small patch of skin on the inside of your arm, if it is your first time usineg this cream.

Stop Use

if irritation or allergic reactions develop.

Ask Doctor

if irritation or allergic reactions develop.If pregnant or breast-feeding, ask a health professional before use

Keep Oot Of Reach Of Children

In case of accidental ingestion, seek medical advice immediately or contact a Poison Control Center right away.

Directions

After cleansing,gently massage a pea-sized amount of cream onto the affected area.Use twice a day, in the morning and evening.

Other information

store in a cool dry place, away from direct sunlight.

Inactive ingredients

Water (Aqua), Mineral Oil (Paraffinum Liquidum), PEG-20 Methyl Glucose Sesquistearate, Glycerin,C13-14 lsoparaffin, Cetyl Alcohol, Methyl Glucose Sesquistarate,Phenoxyethanol, Methyl Paraben